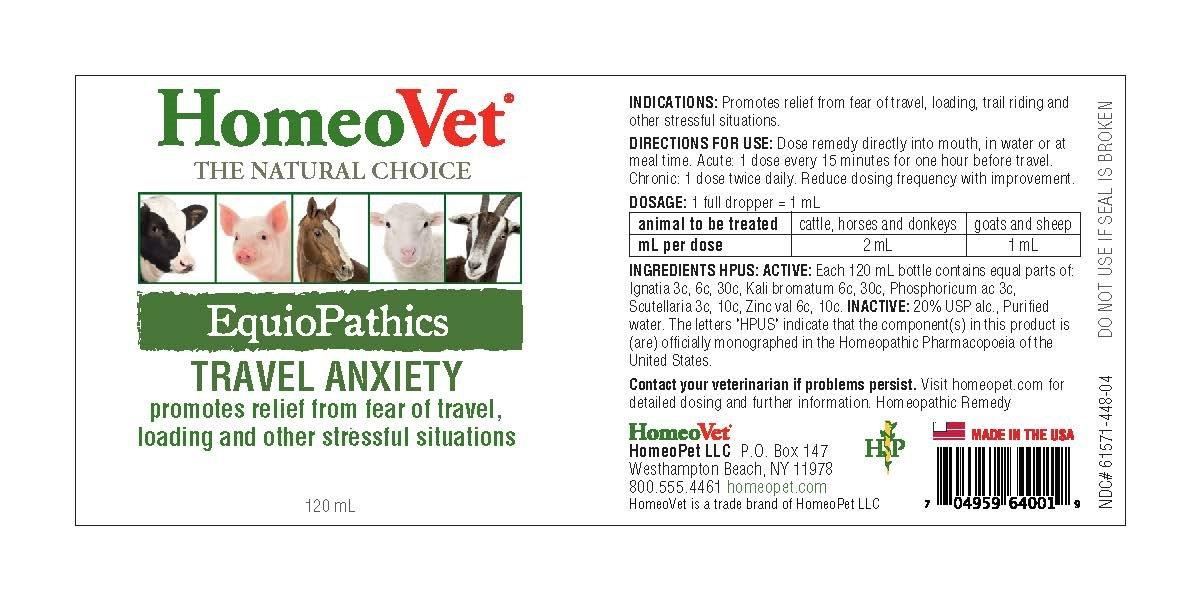 DRUG LABEL: EquioPathics Travel Anxiety
NDC: 61571-448 | Form: LIQUID
Manufacturer: HomeoPet, LLC
Category: homeopathic | Type: OTC ANIMAL DRUG LABEL
Date: 20201202

ACTIVE INGREDIENTS: PHOSPHORIC ACID 3 [hp_C]/120 mL; STRYCHNOS IGNATII SEED 3 [hp_C]/120 mL; ZINC VALERATE DIHYDRATE 6 [hp_C]/120 mL; POTASSIUM BROMIDE 6 [hp_C]/120 mL; SCUTELLARIA LATERIFLORA 3 [hp_C]/120 mL
INACTIVE INGREDIENTS: ALCOHOL; WATER

EquioPathics Travel Anxiety

EquioPathics Travel Anxiety

Promotes relief from fear of travel, loading and other stressful situations.

DIRECTIONS FOR USE AND DOSAGE

Dose remedy directly into mouth, in water or at meal time. Acute 1 dose every 15 minutes for one hour before travel. Chronic: 1 dose twice daily. reduce dosing frequency with improvement.

1 full dropper = 1 mL

animal to be treated | cattle, horses and donkeys | goats and sheep
mL per dose | 2 mL | 1 mL

INDICATIONS

Promotes relief from fear of travel, loading, trail riding and other stressful situations.

Ingredients HPUS

Ignatia 3c, 6c, 30c, Kali bromatum 6c, 30c, Phosphoricum ac 3c, Scutellaria 3c, 10c, Zinc val 6c, 10c

Inactive Ingredients

Alcohol and Purified Water.